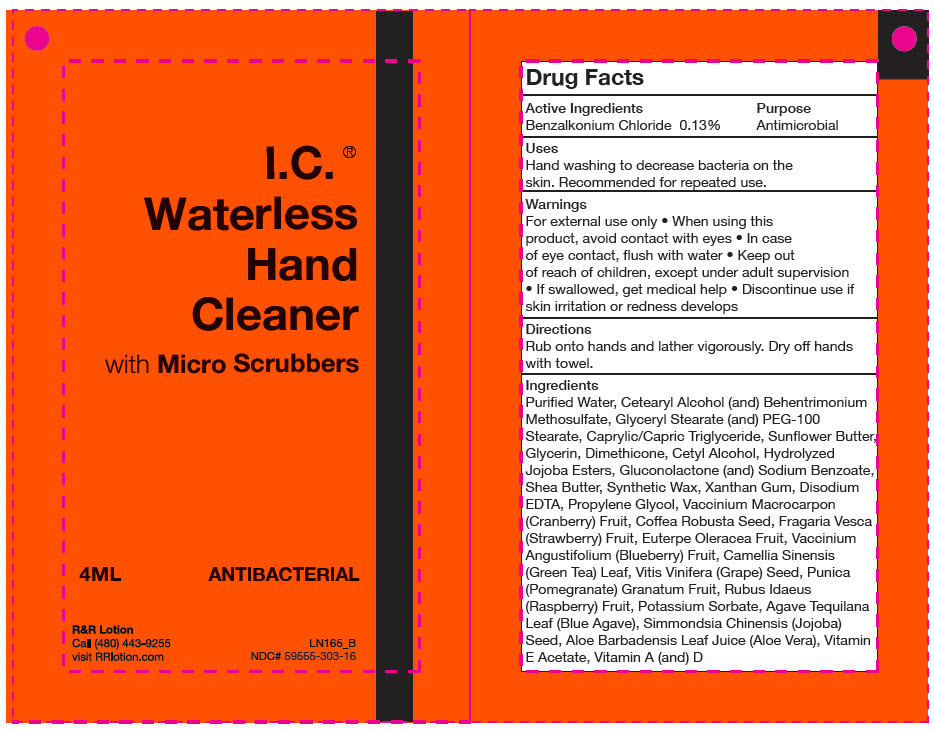 DRUG LABEL: I.C. Waterless Hand Cleaner with Micro Scrubbers
NDC: 59555-303 | Form: LOTION
Manufacturer: R & R Lotion, Inc
Category: otc | Type: HUMAN OTC DRUG LABEL
Date: 20250915

ACTIVE INGREDIENTS: Benzalkonium Chloride 1.3 mg/1 mL
INACTIVE INGREDIENTS: Water; CETOSTEARYL ALCOHOL; Behentrimonium Methosulfate; GLYCERYL MONOSTEARATE; PEG-100 MONOSTEARATE; MEDIUM-CHAIN TRIGLYCERIDES; HELIANTHUS ANNUUS SEED WAX; Glycerin; Dimethicone; Cetyl Alcohol; POTASSIUM HYDROLYZED JOJOBA ESTERS; Gluconolactone; Sodium Benzoate; Shea Butter; Paraffin; Xanthan Gum; EDETATE DISODIUM; PROPYLENE GLYCOL; CRANBERRY; ROBUSTA COFFEE BEAN; FRAGARIA VESCA FRUIT; ACAI; LOWBUSH BLUEBERRY; GREEN TEA LEAF; VITIS VINIFERA SEED PROANTHOCYANIDINS; POMEGRANATE; RASPBERRY; POTASSIUM SORBATE; AGAVE TEQUILANA LEAF; SIMMONDSIA CHINENSIS SEED; ALOE VERA LEAF JUICE; .ALPHA.-TOCOPHEROL ACETATE; VITAMIN A PALMITATE; Cholecalciferol

I.C.® Waterless Hand Cleaner with Micro Scrubbers

Drug Facts

Active Ingredients

Benzalkonium Chloride 0.13%

Purpose

Antimicrobial

Uses

Hand washing to decrease bacteria on the skin. Recommended for repeated use.

Warnings

For external use only

- When using this product, avoid contact with eyes
- In case of eye contact, flush with water

- Keep out of reach of children, except under adult supervision
- If swallowed, get medical help

- Discontinue use if skin irritation or redness develops

Directions

Rub onto hands and lather vigorously. Dry off hands with towel.

Ingredients

Purified Water, Cetearyl Alcohol (and) Behentrimonium Methosulfate, Glyceryl Stearate (and) PEG-100 Stearate, Caprylic/Capric Triglyceride, Sunflower Butter, Glycerin, Dimethicone, Cetyl Alcohol, Hydrolyzed Jojoba Esters, Gluconolactone (and) Sodium Benzoate, Shea Butter, Synthetic Wax, Xanthan Gum, Disodium EDTA, Propylene Glycol, Vaccinium Macrocarpon (Cranberry) Fruit, Coffea Robusta Seed, Fragaria Vesca (Strawberry) Fruit, Euterpe Oleracea Fruit, Vaccinium Angustifolium (Blueberry) Fruit, Camellia Sinensis (Green Tea) Leaf, Vitis Vinifera (Grape) Seed, Punica (Pomegranate) Granatum Fruit, Rubus Idaeus (Raspberry) Fruit, Potassium Sorbate, Agave Tequilana Leaf (Blue Agave), Simmondsia Chinensis (Jojoba) Seed, Aloe Barbadensis Leaf Juice (Aloe Vera), Vitamin E Acetate, Vitamin A (and) D

PRINCIPAL DISPLAY PANEL - 4 mL Packet Label

I.C. ®
Waterless
Hand
Cleaner
with Micro Scrubbers

4ML
ANTIBACTERIAL

R&R Lotion
Call (480) 443-9255
visit RRlotion.com

LN165_B
NDC# 59555-303-16